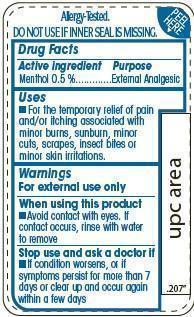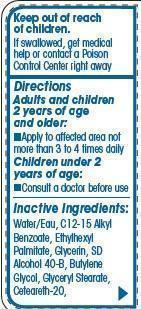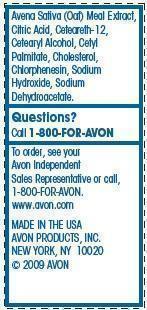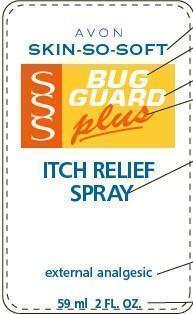 DRUG LABEL: skin so soft bug guard plusitch relief 
    
NDC: 10096-0282 | Form: SPRAY
Manufacturer: Avon Products, Inc.
Category: otc | Type: HUMAN OTC DRUG LABEL
Date: 20120618

ACTIVE INGREDIENTS: Menthol 5 mg/1 mL

Drug Facts

Active ingredient
Menthol 0.5 %......

Purpose
.........External Analgesic

Uses
For the temporary relief of pain and/or itching associated with minor burns, sunburn, minor cuts, scrapes, insect bites or minor skin irritations.

Warnings
For external use only

When using this product

- Avoid contact with eyes. If contact occurs, rinse with water to remove

Stop use and ask a doctor if

- If condition worsens, or if symptoms persist for more than 7 days or clear up and occur again within a few days

Keep out of reach of children. If swallowed, get medical help or contact a Poison Control Center right away

Directions
Adults and children 2 years of age and older:

- Apply to affected area not more than 3 to 4 times daily

Children under 2 years of age:

- Consult a doctor before use

Inactive Ingredients:
Water/Eau, C12-15 Alkyl Benzoate, Ethylhexyl Palmitate, Glycerin, SD Alcohol 40-B, Butylene Glycol, Glyceryl Stearate, Ceteareth-20,Avena Sativa (Oat) Meal Extract, Citric Acid, Ceteareth-12, Cetearyl Alcohol, Cetyl Palmitate, Cholesterol, Chlorphenesin, Sodium Hydroxide, Sodium Dehydroacetate.

Questions?
Call 1-800-FOR-AVON